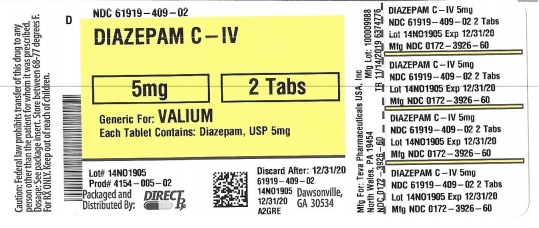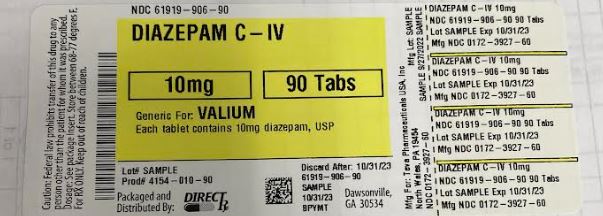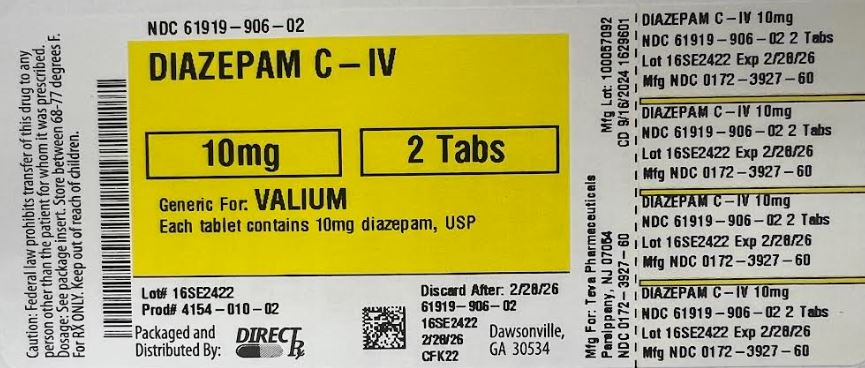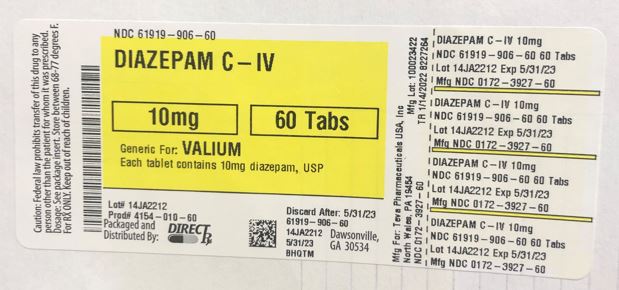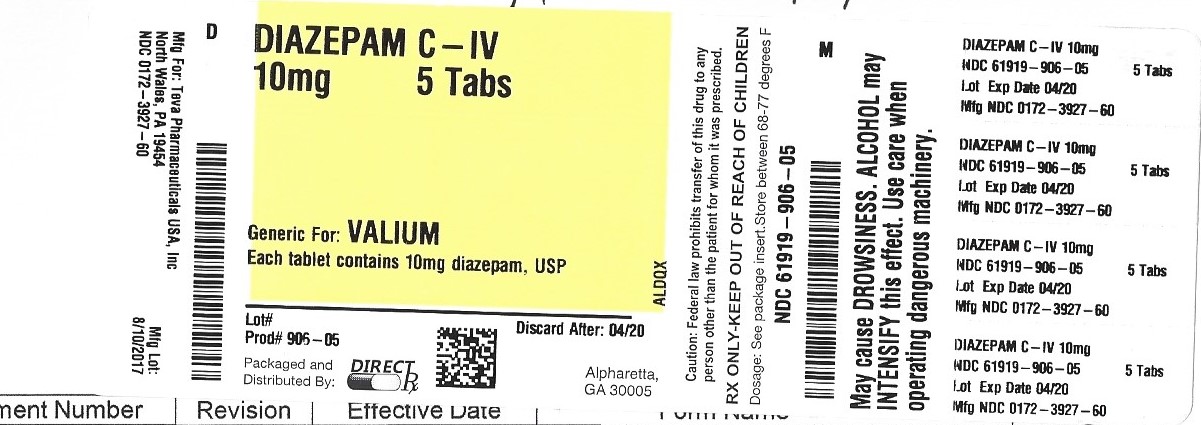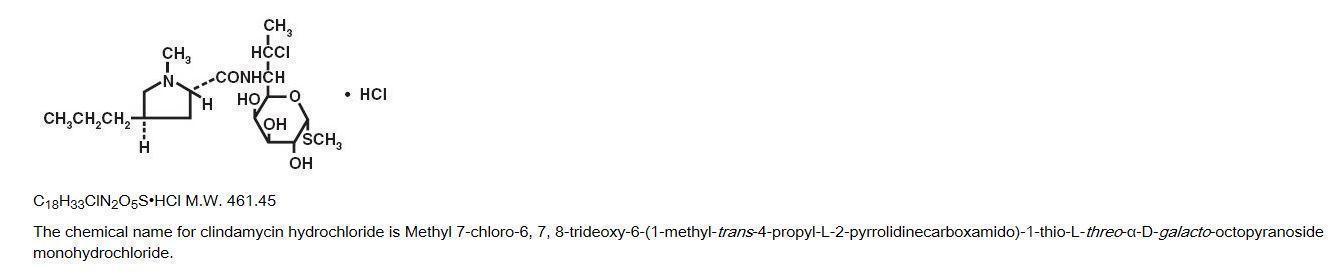 DRUG LABEL: DIAZEPAM
NDC: 61919-906 | Form: TABLET
Manufacturer: Direct_Rx
Category: prescription | Type: HUMAN PRESCRIPTION DRUG LABEL
Date: 20260108
DEA Schedule: CIV

ACTIVE INGREDIENTS: DIAZEPAM 10 mg/1 1
INACTIVE INGREDIENTS: CALCIUM STEARATE; SILICON DIOXIDE; GALACTOSE MONOHYDRATE; CELLULOSE, MICROCRYSTALLINE; LACTOSE MONOHYDRATE

DIAZEPAM

DESCRIPTION SECTION

CIV

Diazepam is a benzodiazepine derivative. The chemical name of diazepam is 7-chloro-1,3-dihydro-1-methyl-5-phenyl-2H-1,4-benzodiazepin-2-one. It is a colorless to light yellow crystalline compound, insoluble in water. The empirical formula is C16H13ClN2O and the molecular weight is 284.75. The structural formula is as follows:

Diazepam is available for oral administration as tablets containing 2 mg, 5 mg or 10 mg diazepam. In addition to the active ingredient diazepam, each tablet contains the following inactive ingredients: calcium stearate, colloidal silicon dioxide, croscarmellose sodium, lactose monohydrate and microcrystalline cellulose with the following dyes: 5-mg tablets contain D&C Yellow #10 aluminum lake; 10-mg tablets contain FD&C Blue #1 aluminum lake. Diazepam 2-mg tablets contain no dye.

CLINICAL PHARMACOLOGY

Diazepam is a benzodiazepine that exerts anxiolytic, sedative, muscle-relaxant, anticonvulsant and amnestic effects. Most of these effects are thought to result from a facilitation of the action of gamma aminobutyric acid (GABA), an inhibitory neurotransmitter in the central nervous system.

Pharmacokinetics

Absorption

After oral administration >90% of diazepam is absorbed and the average time to achieve peak plasma concentrations is 1 to 1.5 hours with a range of 0.25 to 2.5 hours. Absorption is delayed and decreased when administered with a moderate fat meal. In the presence of food mean lag times are approximately 45 minutes as compared with 15 minutes when fasting. There is also an increase in the average time to achieve peak concentrations to about 2.5 hours in the presence of food as compared with 1.25 hours when fasting. This results in an average decrease in Cmax of 20% in addition to a 27% decrease in AUC (range 15% to 50%) when administered with food.

Distribution

Diazepam and its metabolites are highly bound to plasma proteins (diazepam 98%). Diazepam and its metabolites cross the blood-brain and placental barriers and are also found in breast milk in concentrations approximately one tenth of those in maternal plasma (days 3 to 9 post-partum). In young healthy males, the volume of distribution at steady-state is 0.8 to 1.0 L/kg. The decline in the plasma concentration-time profile after oral administration is biphasic. The initial distribution phase has a half-life of approximately 1 hour, although it may range up to >3 hours.

Metabolism

Diazepam is N-demethylated by CYP3A4 and 2C19 to the active metabolite N-desmethyldiazepam, and is hydroxylated by CYP3A4 to the active metabolite temazepam. N-desmethyldiazepam and temazepam are both further metabolized to oxazepam. Temazepam and oxazepam are largely eliminated by glucuronidation.

Elimination

The initial distribution phase is followed by a prolonged terminal elimination phase (half-life up to 48 hours). The terminal elimination half-life of the active metabolite N-desmethyldiazepam is up to 100 hours. Diazepam and its metabolites are excreted mainly in the urine, predominantly as their glucuronide conjugates. The clearance of diazepam is 20 to 30 mL/min in young adults. Diazepam accumulates upon multiple dosing and there is some evidence that the terminal elimination half-life is slightly prolonged.

Pharmacokinetics in Special Populations

Children

In children 3 to 8 years old the mean half-life of diazepam has been reported to be 18 hours.

Newborns

In full term infants, elimination half-lives around 30 hours have been reported, with a longer average half-life of 54 hours reported in premature infants of 28 to 34 weeks gestational age and 8 to 81 days post-partum. In both premature and full term infants the active metabolite desmethyldiazepam shows evidence of continued accumulation compared to children. Longer half-lives in infants may be due to incomplete maturation of metabolic pathways.

Geriatric

Elimination half-life increases by approximately 1 hour for each year of age beginning with a half-life of 20 hours at 20 years of age. This appears to be due to an increase in volume of distribution with age and a decrease in clearance. Consequently, the elderly may have lower peak concentrations, and on multiple dosing higher trough concentrations. It will also take longer to reach steady-state. Conflicting information has been published on changes of plasma protein binding in the elderly. Reported changes in free drug may be due to significant decreases in plasma proteins due to causes other than simply aging.

Hepatic Insufficiency

In mild and moderate cirrhosis, average half-life is increased. The average increase has been variously reported from 2-fold to 5-fold, with individual half-lives over 500 hours reported. There is also an increase in volume of distribution, and average clearance decreases by almost half. Mean half-life is also prolonged with hepatic fibrosis to 90 hours (range 66 to 104 hours), with chronic active hepatitis to 60 hours (range 26 to 76 hours), and with acute viral hepatitis to 74 hours (range 49 to 129). In chronic active hepatitis, clearance is decreased by almost half.

INDICATIONS & USAGE SECTION

Diazepam tablets are indicated for the management of anxiety disorders or for the short-term relief of the symptoms of anxiety. Anxiety or tension associated with the stress of everyday life usually does not require treatment with an anxiolytic.

In acute alcohol withdrawal, diazepam may be useful in the symptomatic relief of acute agitation, tremor, impending or acute delirium tremens and hallucinosis.

Diazepam is a useful adjunct for the relief of skeletal muscle spasm due to reflex spasm to local pathology (such as inflammation of the muscles or joints, or secondary to trauma); spasticity caused by upper motor neuron disorders (such as cerebral palsy and paraplegia); athetosis; and stiff-man syndrome.

Oral diazepam may be used adjunctively in convulsive disorders, although it has not proved useful as the sole therapy.

The effectiveness of diazepam in long-term use, that is, more than 4 months, has not been assessed by systematic clinical studies. The physician should periodically reassess the usefulness of the drug for the individual patient.

CONTRAINDICATIONS SECTION

Diazepam tablets are contraindicated in patients with a known hypersensitivity to diazepam and, because of the lack of sufficient clinical experience, in pediatric patients under 6 months of age. Diazepam is also contraindicated in patients with myasthenia gravis, severe respiratory insufficiency, severe hepatic insufficiency, and sleep apnea syndrome. It may be used in patients with open-angle glaucoma who are receiving appropriate therapy, but is contraindicated in acute narrow-angle glaucoma.

WARNINGS SECTION

Diazepam is not recommended in the treatment of psychotic patients and should not be employed instead of appropriate treatment.

Since diazepam has a central nervous system depressant effect, patients should be advised against the simultaneous ingestion of alcohol and other CNS-depressant drugs during diazepam therapy.

As with other agents that have anticonvulsant activity, when diazepam is used as an adjunct in treating convulsive disorders, the possibility of an increase in the frequency and/or severity of grand mal seizures may require an increase in the dosage of standard anticonvulsant medication. Abrupt withdrawal of diazepam in such cases may also be associated with a temporary increase in the frequency and/or severity of seizures.

Pregnancy

An increased risk of congenital malformations and other developmental abnormalities associated with the use of benzodiazepine drugs during pregnancy has been suggested. There may also be non-teratogenic risks associated with the use of benzodiazepines during pregnancy. There have been reports of neonatal flaccidity, respiratory and feeding difficulties, and hypothermia in children born to mothers who have been receiving benzodiazepines late in pregnancy. In addition, children born to mothers receiving benzodiazepines on a regular basis late in pregnancy may be at some risk of experiencing withdrawal symptoms during the postnatal period.

Diazepam has been shown to be teratogenic in mice and hamsters when given orally at daily doses of 100 mg/kg or greater (approximately eight times the maximum recommended human dose [MRHD=1 mg/kg/day] or greater on a mg/m2 basis). Cleft palate and encephalopathy are the most common and consistently reported malformations produced in these species by administration of high, maternally toxic doses of diazepam during organogenesis. Rodent studies have indicated that prenatal exposure to diazepam doses similar to those used clinically can produce long-term changes in cellular immune responses, brain neurochemistry, and behavior.

In general, the use of diazepam in women of childbearing potential, and more specifically during known pregnancy, should be considered only when the clinical situation warrants the risk to the fetus. The possibility that a woman of childbearing potential may be pregnant at the time of institution of therapy should be considered. If this drug is used during pregnancy, or if the patient becomes pregnant while taking this drug, the patient should be apprised of the potential hazard to the fetus. Patients should also be advised that if they become pregnant during therapy or intend to become pregnant they should communicate with their physician about the desirability of discontinuing the drug.

Labor and Delivery

Special care must be taken when diazepam is used during labor and delivery, as high single doses may produce irregularities in the fetal heart rate and hypotonia, poor sucking, hypothermia, and moderate respiratory depression in the neonates. With newborn infants it must be remembered that the enzyme system involved in the breakdown of the drug is not yet fully developed (especially in premature infants).

Nursing Mothers

Diazepam passes into breast milk. Breastfeeding is therefore not recommended in patients receiving diazepam.

PRECAUTIONS SECTION

General

If diazepam is to be combined with other psychotropic agents or anticonvulsant drugs, careful consideration should be given to the pharmacology of the agents to be employed—particularly with known compounds that may potentiate the action of diazepam, such as phenothiazines, narcotics, barbiturates, MAO inhibitors and other antidepressants (see Drug Interactions).

The usual precautions are indicated for severely depressed patients or those in whom there is any evidence of latent depression or anxiety associated with depression, particularly the recognition that suicidal tendencies may be present and protective measures may be necessary.

Psychiatric and paradoxical reactions are known to occur when using benzodiazepines (see ADVERSE REACTIONS). Should this occur, use of the drug should be discontinued. These reactions are more likely to occur in children and the elderly.

A lower dose is recommended for patients with chronic respiratory insufficiency, due to the risk of respiratory depression.

Benzodiazepines should be used with extreme caution in patients with a history of alcohol or drug abuse (see DRUG ABUSE AND DEPENDENCE).

In debilitated patients, it is recommended that the dosage be limited to the smallest effective amount to preclude the development of ataxia or oversedation (2 mg to 2.5 mg once or twice daily, initially, to be increased gradually as needed and tolerated).

Some loss of response to the effects of benzodiazepines may develop after repeated use of diazepam for a prolonged time.

Information for Patients

To assure the safe and effective use of benzodiazepines, patients should be informed that, since benzodiazepines may produce psychological and physical dependence, it is advisable that they consult with their physician before either increasing the dose or abruptly discontinuing this drug. The risk of dependence increases with duration of treatment; it is also greater in patients with a history of alcohol or drug abuse.

Patients should be advised against the simultaneous ingestion of alcohol and other CNS-depressant drugs during diazepam therapy. As is true of most CNS-acting drugs, patients receiving diazepam should be cautioned against engaging in hazardous occupations requiring complete mental alertness, such as operating machinery or driving a motor vehicle.

Drug Interactions

Centrally Acting Agents

If diazepam is to be combined with other centrally acting agents, careful consideration should be given to the pharmacology of the agents employed particularly with compounds that may potentiate or be potentiated by the action of diazepam, such as phenothiazines, antipsychotics, anxiolytics/sedatives, hypnotics, anticonvulsants, narcotic analgesics, anesthetics, sedative antihistamines, narcotics, barbiturates, MAO inhibitors and other antidepressants.

Alcohol

Concomitant use with alcohol is not recommended due to enhancement of the sedative effect.

Antacids

Diazepam peak concentrations are 30% lower when antacids are administered concurrently. However, there is no effect on the extent of absorption. The lower peak concentrations appear due to a slower rate of absorption, with the time required to achieve peak concentrations on average 20 to 25 minutes greater in the presence of antacids. However, this difference was not statistically significant.

Compounds Which Inhibit Certain Hepatic Enzymes

There is a potentially relevant interaction between diazepam and compounds which inhibit certain hepatic enzymes (particularly cytochrome P450 3A and 2C19). Data indicate that these compounds influence the pharmacokinetics of diazepam and may lead to increased and prolonged sedation. At present, this reaction is known to occur with cimetidine, ketoconazole, fluvoxamine, fluoxetine, and omeprazole.

Phenytoin

There have also been reports that the metabolic elimination of phenytoin is decreased by diazepam.

Carcinogenesis, Mutagenesis, Impairment of Fertility

In studies in which mice and rats were administered diazepam in the diet at a dose of 75 mg/kg/day (approximately 6 and 12 times, respectively, the maximum recommended human dose [MRHD=1 mg/kg/day] on a mg/m2 basis) for 80 and 104 weeks, respectively, an increased incidence of liver tumors was observed in males of both species. The data currently available are inadequate to determine the mutagenic potential of diazepam. Reproduction studies in rats showed decreases in the number of pregnancies and in the number of surviving offspring following administration of an oral dose of 100 mg/kg/day (approximately 16 times the MRHD on a mg/m2 basis) prior to and during mating and throughout gestation and lactation. No adverse effects on fertility or offspring viability were noted at a dose of 80 mg/kg/day (approximately 13 times the MRHD on a mg/m2 basis).

Pregnancy
Category D

(see WARNINGS: Pregnancy).

Pediatric Use

Safety and effectiveness in pediatric patients below the age of 6 months have not been established.

Geriatric Use

In elderly patients, it is recommended that the dosage be limited to the smallest effective amount to preclude the development of ataxia or oversedation (2 mg to 2.5 mg once or twice daily, initially to be increased gradually as needed and tolerated).

Extensive accumulation of diazepam and its major metabolite, desmethyldiazepam, has been noted following chronic administration of diazepam in healthy elderly male subjects. Metabolites of this drug are known to be substantially excreted by the kidney, and the risk of toxic reactions may be greater in patients with impaired renal function. Because elderly patients are more likely to have decreased renal function, care should be taken in dose selection, and it may be useful to monitor renal function.

Hepatic Insufficiency

Decreases in clearance and protein binding, and increases in volume of distribution and half-life has been reported in patients with cirrhosis. In such patients, a 2- to 5- fold increase in mean half-life has been reported. Delayed elimination has also been reported for the active metabolite desmethyldiazepam. Benzodiazepines are commonly implicated in hepatic encephalopathy. Increases in half-life have also been reported in hepatic fibrosis and in both acute and chronic hepatitis (see CLINICAL PHARMACOLOGY: Pharmacokinetics in Special Populations: Hepatic Insufficiency).

ADVERSE REACTIONS SECTION

Side effects most commonly reported were drowsiness, fatigue, muscle weakness, and ataxia. The following have also been reported:

Central Nervous System: confusion, depression, dysarthria, headache, slurred speech, tremor, vertigo

Gastrointestinal System: constipation, nausea, gastrointestinal disturbances

Special Senses: blurred vision, diplopia, dizziness

Cardiovascular System: hypotension

Psychiatric and Paradoxical Reactions: stimulation, restlessness, acute hyperexcited states, anxiety, agitation, aggressiveness, irritability, rage, hallucinations, psychoses, delusions, increased muscle spasticity, insomnia, sleep disturbances, and nightmares. Inappropriate behavior and other adverse behavioral effects have been reported when using benzodiazepines. Should these occur, use of the drug should be discontinued. They are more likely to occur in children and in the elderly.

Urogenital System: incontinence, changes in libido, urinary retention

Skin and Appendages: skin reactions

Laboratories: elevated transaminases and alkaline phosphatase

Other: changes in salivation, including dry mouth, hypersalivation

Antegrade amnesia may occur using therapeutic dosages, the risk increasing at higher dosages. Amnestic effects may be associated with inappropriate behavior.

Minor changes in EEG patterns, usually low-voltage fast activity, have been observed in patients during and after diazepam therapy and are of no known significance.

Because of isolated reports of neutropenia and jaundice, periodic blood counts and liver function tests are advisable during long-term therapy.

Postmarketing Experience:

Injury, Poisoning and Procedural Complications: There have been reports of falls and fractures in benzodiazepine users. The risk is increased in those taking concomitant sedatives (including alcohol), and in the elderly.

DRUG ABUSE AND DEPENDENCE SECTION

Diazepam is subject to Schedule IV control under the Controlled Substances Act of 1970. Abuse and dependence of benzodiazepines have been reported. Addiction-prone individuals (such as drug addicts or alcoholics) should be under careful surveillance when receiving diazepam or other psychotropic agents because of the predisposition of such patients to habituation and dependence. Once physical dependence to benzodiazepines has developed, termination of treatment will be accompanied by withdrawal symptoms. The risk is more pronounced in patients on long-term therapy.

Withdrawal symptoms, similar in character to those noted with barbiturates and alcohol have occurred following abrupt discontinuance of diazepam. These withdrawal symptoms may consist of tremor, abdominal and muscle cramps, vomiting, sweating, headache, muscle pain, extreme anxiety, tension, restlessness, confusion and irritability. In severe cases, the following symptoms may occur: derealization, depersonalization, hyperacusis, numbness and tingling of the extremities, hypersensitivity to light, noise and physical contact, hallucinations or epileptic seizures. The more severe withdrawal symptoms have usually been limited to those patients who had received excessive doses over an extended period of time. Generally milder withdrawal symptoms (e.g., dysphoria and insomnia) have been reported following abrupt discontinuance of benzodiazepines taken continuously at therapeutic levels for several months. Consequently, after extended therapy, abrupt discontinuation should generally be avoided and a gradual dosage tapering schedule followed.

Chronic use (even at therapeutic doses) may lead to the development of physical dependence: discontinuation of the therapy may result in withdrawal or rebound phenomena.

Rebound Anxiety:

A transient syndrome whereby the symptoms that led to treatment with diazepam recur in an enhanced form. This may occur upon discontinuation of treatment. It may be accompanied by other reactions including mood changes, anxiety, and restlessness.

Since the risk of withdrawal phenomena and rebound phenomena is greater after abrupt discontinuation of treatment, it is recommended that the dosage be decreased gradually.

OVERDOSAGE SECTION

Overdose of benzodiazepines is usually manifested by central nervous system depression ranging from drowsiness to coma. In mild cases, symptoms include drowsiness, confusion, and lethargy. In more serious cases, symptoms may include ataxia, diminished reflexes, hypotonia, hypotension, respiratory depression, coma (rarely), and death (very rarely). Overdose of benzodiazepines in combination with other CNS depressants (including alcohol) may be fatal and should be closely monitored.

Management of Overdosage

Following overdose with oral benzodiazepines, general supportive measures should be employed including the monitoring of respiration, pulse, and blood pressure. Vomiting should be induced (within 1 hour) if the patient is conscious. Gastric lavage should be undertaken with the airway protected if the patient is unconscious. Intravenous fluids should be administered. If there is no advantage in emptying the stomach, activated charcoal should be given to reduce absorption. Special attention should be paid to respiratory and cardiac function in intensive care. General supportive measures should be employed, along with intravenous fluids, and an adequate airway maintained. Should hypotension develop, treatment may include intravenous fluid therapy, repositioning, judicious use of vasopressors appropriate to the clinical situation, if indicated, and other appropriate countermeasures. Dialysis is of limited value.

As with the management of intentional overdosage with any drug, it should be considered that multiple agents may have been ingested.

Flumazenil, a specific benzodiazepine-receptor antagonist, is indicated for the complete or partial reversal of the sedative effects of benzodiazepines and may be used in situations when an overdose with a benzodiazepine is known or suspected. Prior to the administration of flumazenil, necessary measures should be instituted to secure airway, ventilation and intravenous access. Flumazenil is intended as an adjunct to, not as a substitute for, proper management of benzodiazepine overdose. Patients treated with flumazenil should be monitored for resedation, respiratory depression and other residual benzodiazepine effects for an appropriate period after treatment. The prescriber should be aware of a risk of seizure in association with flumazenil treatment, particularly in long-term benzodiazepine users and in cyclic antidepressant overdose. Caution should be observed in the use of flumazenil in epileptic patients treated with benzodiazepines. The complete flumazenil package insert, including CONTRAINDICATIONS, WARNINGS, and PRECAUTIONS, should be consulted prior to use.

Withdrawal symptoms of the barbiturate type have occurred after the discontinuation of benzodiazepines (see DRUG ABUSE AND DEPENDENCE).

DOSAGE & ADMINISTRATIVE SECTION

Dosage should be individualized for maximum beneficial effect. While the usual daily dosages given below will meet the needs of most patients, there will be some who may require higher doses. In such cases, dosage should be increased cautiously to avoid adverse effects.

HOW SUPPLIED SECTION

For oral administration, Diazepam Tablets, USP are supplied as:

2 mg- white, flat-faced beveled edge scored tablets, debossed "2682" on one side and "V" on the reverse side, supplied in bottles of 10, 30, 60, 100, 500, 1000 and 5000.

5 mg- yellow, flat-faced beveled edge scored tablets, debossed "2683" on one side and "V" on the reverse side, supplied in bottles of 10, 30, 60, 90, 100, 120, 500, 1000 and 5000.

10 mg- blue, flat-faced beveled edge scored tablets, debossed "2684" on one side and "V" on the reverse side, supplied in bottles of 10, 30, 60, 90, 100, 120, 500, 1000 and 5000.

STORAGE AND HANDLING SECTION

Store at 20°-25°C (68°-77°F) [see USP Controlled Room Temperature].

Dispense in tight, light-resistant containers as defined in USP/NF.

Manufactured for:
QUALITEST PHARMACEUTICALS
Huntsville, AL 35811

8181922
Rev 1/14
R4